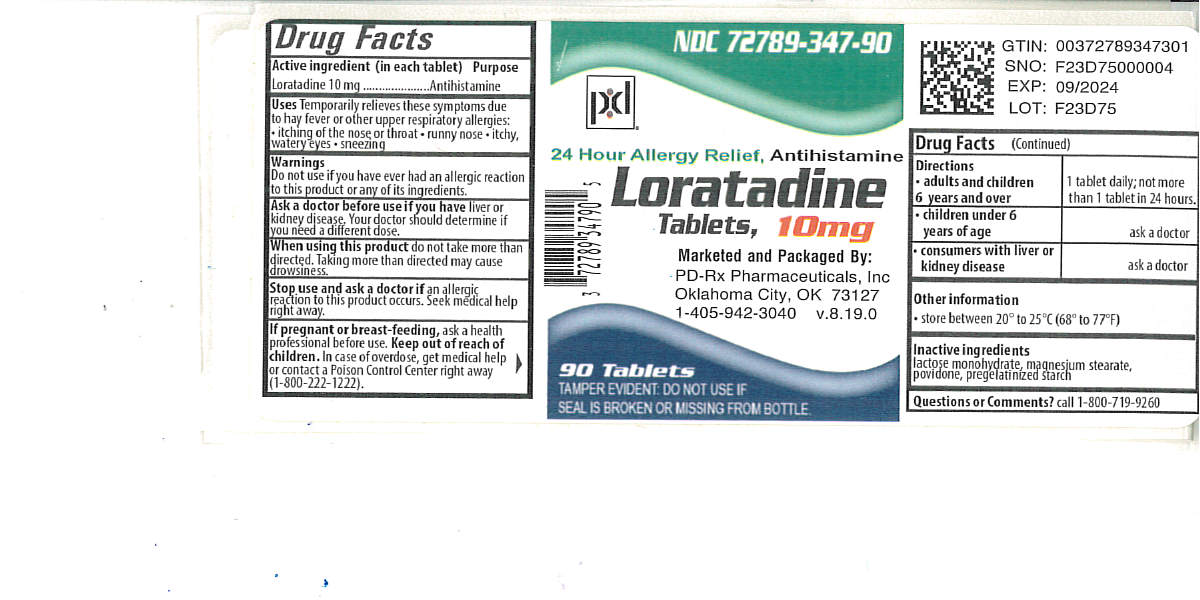 DRUG LABEL: Loratadine
NDC: 72789-347 | Form: TABLET
Manufacturer: PD-Rx Pharmaceuticals, Inc.
Category: otc | Type: HUMAN OTC DRUG LABEL
Date: 20260226

ACTIVE INGREDIENTS: LORATADINE 10 mg/1 1
INACTIVE INGREDIENTS: LACTOSE MONOHYDRATE; MAGNESIUM STEARATE; POVIDONE, UNSPECIFIED

Loratadine Tablets, 10 mg Drug Facts

Active ingredient (in each tablet)

Loratadine 10 mg

Purpose

Antihistamine

Uses

temporarily relieves these symptoms due to hay fever or other upper respiratory allergies:

- runny nose
- itchy, watery eyes
- sneezing
- itching of the nose or throat

Warnings

Do not use

if you have ever had an allergic reaction to this product or any of its ingredients

Ask a doctor before use if you have

liver or kidney disease. Your doctor should determine if you need a different dose.

When using this product

do not take more than directed. Taking more than directed may cause drowsiness.

Stop use and ask a doctor if

an allergic reaction to this product occurs. Seek medical help right away.

If pregnant or breast-feeding,

ask a health professional before use.

Keep out of reach of children.

In case of overdose, get medical help or contact a Poison Control Center right away. (1-800-222-1222)

Directions

adults and children 6 years and over | 1 tablet daily; not more than 1 tablet in 24 hours
children under 6 years of age | ask a doctor
consumers with liver or kidney disease | ask a doctor

Other information

- do not use if printed foil under cap is broken or missing
- store between 20° to 25°C (68° to 77°F)

Inactive ingredients

lactose monohydrate, magnesium stearate, povidone, pregelatinized starch

Questions or comments?

1-800-719-9260

Principal Display Panel

Loratadine Tablets, 10 mg

Antihistamine

24 Hour Relief of: